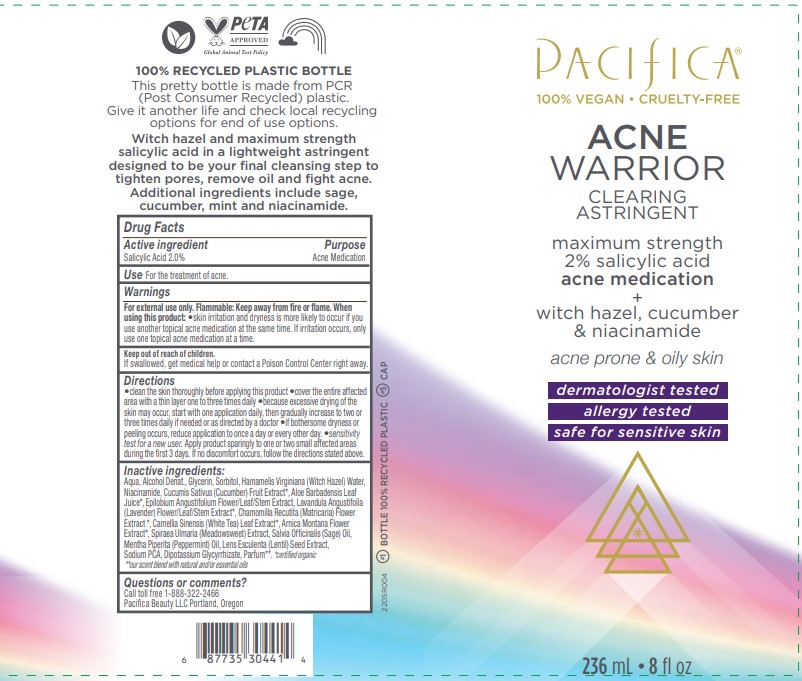 DRUG LABEL: Acne Warrior Clearing Astringent
NDC: 61197-121 | Form: LIQUID
Manufacturer: Pacifica Beauty, LLC
Category: otc | Type: HUMAN OTC DRUG LABEL
Date: 20250103

ACTIVE INGREDIENTS: SALICYLIC ACID 2 g/100 mL
INACTIVE INGREDIENTS: ALOE VERA LEAF; WATER; LAVANDULA ANGUSTIFOLIA WHOLE; CHAMOMILE FLOWER OIL; HAMAMELIS VIRGINIANA LEAF WATER; EPILOBIUM ANGUSTIFOLIUM WHOLE; SALVIA OFFICINALIS WHOLE; SODIUM PYRROLIDONE CARBOXYLATE; ALCOHOL; GLYCERIN; SORBITOL; NIACINAMIDE; CUCUMIS SATIVUS WHOLE; LENTIL; CAMELLIA SINENSIS WHOLE; ARNICA MONTANA FLOWER; MENTHA PIPERITA; GLYCYRRHIZINATE DIPOTASSIUM

Acne Warrior Clearing Astringent

Active ingredient Purpose

Salicylic Acid 2.0% Acne Medication

Use

For the treatment of acne.

Warnings

For external use only. Flammable: Keep away from fire or flame. When using this product: skin irritation and dryness is more likely to occur if you use another topical acne medication at the same time. If irritation occurs, only use one topical acne medication at a time.

When using this product: skin irritation and dryness is more likely to occur if you use another topical acne medication at the same time. If irritation occurs, only use one topical acne medication at a time.

Keep out of reach of children. If swallowed, get medical help or contact a Poison Control Center right away.

Directions

Clean the skin thoroughly before applying this product. Cover the entire affected area with a thin layer one to three times daily. Because excessive drying of the skin may occur, start with one application daily, then gradually increase to two or three times daily if needed or as directed by a doctor. If bothersome dryness or peeling occurs, reduce application to once a day or every other day. Sensitivity test for a new user. Apply product sparingly to one or two small affected areas during the first 3 days. If no discomfort occurs, follow the directions stated above.

Inactive ingredients:

Aqua, Alcohol Denat., Glycerin, Sorbitol, Hamamelis Virginiana (Witch Hazel) Water, Niacinamide, Cucumis Sativus (Cucumber) Fruit Extract*, Aloe Barbadensis Leaf Juice*, Epilobium Angustifolium Flower/Leaf/Stem Extract, Lavandula Angustifolia (Lavender) Flower/Leaf/Stem Extract*, Chamomilla Recutita (Matricaria) Flower Extract *, Camellia Sinensis (White Tea) Leaf Extract*, Arnica Montana Flower Extract*, Spiraea Ulmaria (Meadowsweet) Extract, Salvia Officinalis (Sage) Oil, Mentha Piperita (Peppermint) Oil, Lens Esculenta (Lentil) Seed Extract, Sodium PCA, Dipotassium Glycyrrhizate, Parfum**. *certified organic **our scent blend with natural and/or essential oils

Questions or comments?

Call toll free 1-888-322-2466
Pacifica Beauty LLC Portland, Oregon